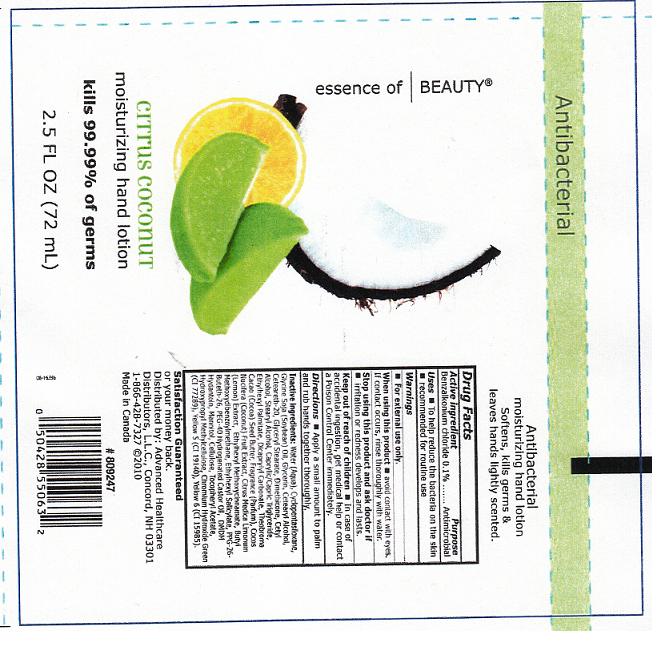 DRUG LABEL: MOISTURIZING HAND 
NDC: 59779-331 | Form: LOTION
Manufacturer: CVS PHARMACY
Category: otc | Type: HUMAN OTC DRUG LABEL
Date: 20110518

ACTIVE INGREDIENTS: BENZALKONIUM CHLORIDE 0.1 mL/100 mL
INACTIVE INGREDIENTS: WATER; CYCLOMETHICONE 5; SOYBEAN OIL; GLYCERIN; CETOSTEARYL ALCOHOL; POLYOXYL 20 CETOSTEARYL ETHER; GLYCERYL MONOSTEARATE; DIMETHICONE; CETYL ALCOHOL; STEARYL ALCOHOL; MEDIUM-CHAIN TRIGLYCERIDES; ETHYLHEXYL PALMITATE; DICAPRYLYL CARBONATE; COCOA BUTTER; COCONUT; LEMON; OCTINOXATE; AVOBENZONE; OCTISALATE; POLYOXYL 40 CASTOR OIL; DMDM HYDANTOIN; MANNITOL; POWDERED CELLULOSE; .ALPHA.-TOCOPHEROL ACETATE, D-; HYPROMELLOSES; CHROMIC OXIDE; FD&C YELLOW NO. 5; FD&C YELLOW NO. 6

DRUG FACTS

ACTIVE INGREDIENT

BENZALKONIUM CHLORIDE 0.1 PERCENT

PURPOSE

ANTIMICROBIAL

USES

TO HELP REDUCE BACTERIA ON THE SKIN. RECOMMENDED FOR ROUTINE USE.

WARNINGS

FOR EXTERNAL USE ONLY.

WHEN USING THIS PRODUCT

AVOID CONTACT WITH EYES. IF CONTACT OCCURS, RINSE THOROUGHLY WITH WATER.

STOP USING THIS PRODUCT AND ASK DOCTOR IF

IRRITATION OR REDNESS DEVELOPS AND LASTS.

KEEP OUT OF REACH OF CHILDREN

IN CASE OF ACCIDENTAL INGESTION, GET MEDICAL HELP OR CONTACT A POISON CONTROL CENTER IMMEDIATELY.

DIRECTIONS

APPLY A SMALL AMOUNT TO PALM AND RUB HANDS TOGETHER THOROUGHLY.

INACTIVE INGREDIENTS

WATER, CYCLOPENTASILOXANE, GLYCINE SOJA (SOYBEAN) OIL, GLYCERIN, CETEARYL ALCOHOL, CETEARETH-20, GLYCERYL STEARATE, DIMETHICONE, CETYL ALCOHOL, STEARYL ALCOHOL, CAPRYLIC/CAPRIC TRIGLYCERIDE, ETHYLHEXYL PALMITATE, DICAPRYLYL CARBONATE, THEOBROMA CACAO (COCOA) SEED BUTTER, FRAGRANCE, COCOS NUCIFERA (COCONUT) FRUIT EXTRACT, CITRUS MEDICA LIMONUM (LEMON) EXTRACT, ETHYLHEXYL METHOXYCINNAMATE, BUTYL METHOXYDIBENZOYLMETHANE, ETHYLHEXYL SALICYLATE, PPG-26-BUTETH-26, PEG-40 HYDROGENATED CASTOR OIL, DMDM HYDANTOIN, MANNITOL, CELLULOSE, TOCOPHERYL ACETATE, HYDROXYPROPYL METHYLCELLULOSE, CHROMIUM HYDROXIDE GREEN (CI 77289), YELLOW 5 (CI 19140), YELLOW 10 (CI 47005).